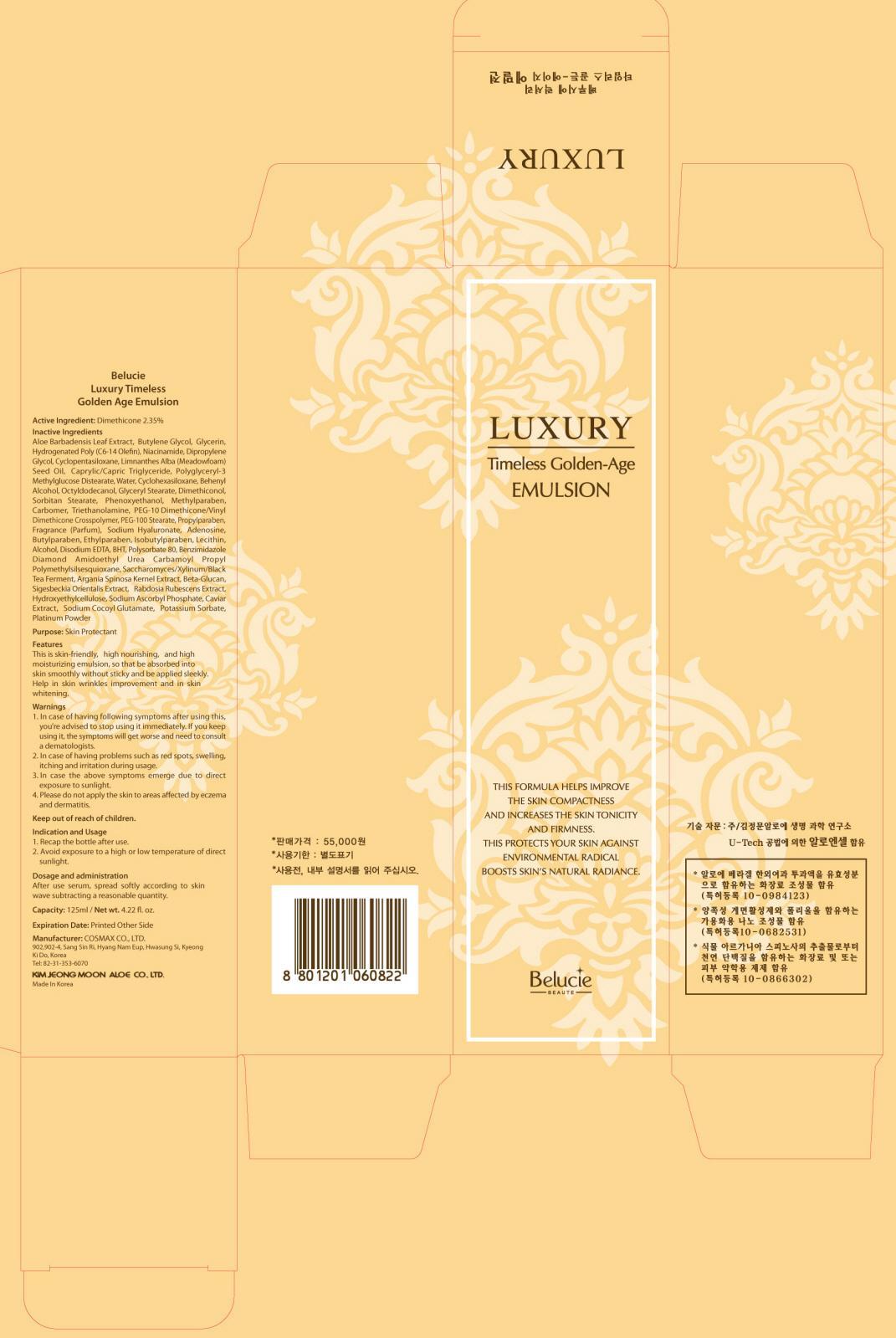 DRUG LABEL: Belucie Luxury Timeless Golden Age Emulsion
NDC: 50410-040 | Form: CREAM
Manufacturer: KIMJEONGMOON ALOE CO., LTD.
Category: otc | Type: HUMAN OTC DRUG LABEL
Date: 20121129

ACTIVE INGREDIENTS: Dimethicone 2.93 g/125 mL
INACTIVE INGREDIENTS: ALOE VERA LEAF; Butylene Glycol; Glycerin; Niacinamide

ACTIVE INGREDIENT

Active Ingredient: Dimethicone 2.35%

INACTIVE INGREDIENT

Inactive Ingredients:

Aloe Barbadensis Leaf Extract, Butylene Glycol, Glycerin, Hydrogenated Poly(C6-14 Olefin), Niacinamide, Dipropylene Glycol, Cyclopentasiloxane, Limnanthes Alba (Meadowfoam) Seed Oil, Caprylic/Capric Triglyceride, Polyglyceryl-3 Methylglucose Distearate, Water, Cyclohexasiloxane, Behenyl Alcohol, Octyldodecanol, Glyceryl Stearate, Dimethiconol, Sorbitan Stearate, Phenoxyethanol, Methylparaben, Carbomer, Triethanolamine, PEG-10 Dimethicone/Vinyl Dimethicone Crosspolymer, PEG-100 Stearate, Propylparaben, Fragrance(Parfum), Sodium Hyaluronate, Adenosine, Butylparaben, Ethylparaben, Isobutylparaben, Lecithin, Alcohol, Disodium EDTA, BHT, Polysorbate 80, Benzimidazole Diamond Amidoethyl Urea Carbamoyl Propyl Polymethylsilsesquioxane, Saccharomyces/Xylinum/Black Tea Ferment, Argania Spinosa Kernel Extract, Beta-Glucan, Sigesbeckia Orientalis Extract, Rabdosia Rubescens Extract, Hydroxyethylcellulose, Sodium Ascorbyl Phosphate, Caviar Extract, Sodium Cocoyl Glutamate, Potassium Sorbate, Platinum Powder

PURPOSE

Purpose: Skin Protectant

WARNINGS

1. In case of having following symptoms after using this, you’re advised to stop using it immediately. If you keep using it, the symptoms will get worse and need to consult a dematologists.
2. In case of having problems such as red spots, swelling, itching and irritation during usage
3. In case the above symptoms emerge due to direct exposure to sunlight
4. Please do not apply the skin to areas affected by eczema and dermatitis

KEEP OUT OF REACH OF CHILDREN

INDICATIONS AND USAGE

Indication and usage
1. Recap the bottle after use.
2. Avoid exposure to a high or low temperature of direct sunlight

DOSAGE AND ADMINISTRATION

After use serum, spread softly according to skin wave subtracting a reasonable quantity.